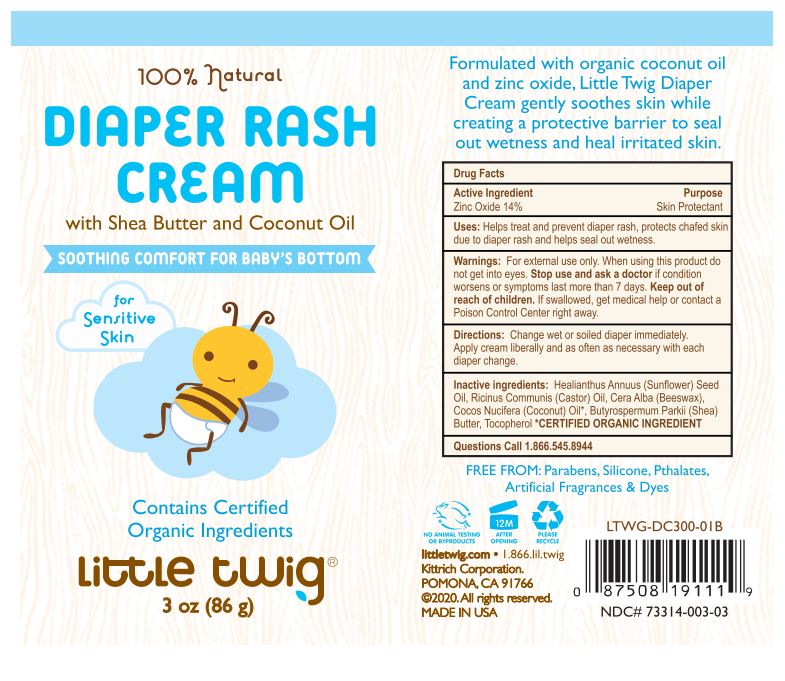 DRUG LABEL: Little Twig Diaper Rash Cream
NDC: 73314-003 | Form: OINTMENT
Manufacturer: Kittrich Corporation
Category: otc | Type: HUMAN OTC DRUG LABEL
Date: 20201231

ACTIVE INGREDIENTS: ZINC OXIDE 14 g/100 g
INACTIVE INGREDIENTS: HELIANTHUS ANNUUS SEED WAX; CASTOR OIL; COCONUT OIL; SHEA BUTTER; WHITE WAX; TOCOPHEROL

Little Twig Diaper Rash Cream

Formulated with organic coconut oil and zinc oxide, Little Twig Diaper Cream gently soothes skin while creating a protective barrier to seal out wetness and heal irritated skin.

Active Ingredient

Active Ingredient: Zinc Oxide 14%

Purpose

Purpose Skin Protectant

Indications & Usage

Uses:

Helps treat and prevent diaper rash, protects chafed skin due to diaper rash and helps seal out wetness.

Warnings

Warnings: For external use only. When using this product do not get into eyes.

Stop Use

Stop use and ask a doctor if condition worsens or symptoms last more than 7 days.

Keep out of reach of children. If swallowed, get medical help or contact a Poison Control Center right away.

Directions

Directions: Change wet or soiled diaper immediately. Apply cream liberally and as often as necessary with each diaper change.

Inactive Ingredients

Healianthus Annuus (Sunflower) Seed Oil, Ricinus Communis (Castor) Oil, Cera Alba (Beeswax), Cocos Nucifera (Coconut) Oil*, Butyrosperumum Parkii (Shea) Butter, Tocopherol *CERTIFIED ORGANIC INGREDIENT

Questions Call 1.866.545.8944

FREE FROM: Parabens, Silicone, Pthalates, Artificial Fragrances & Dyes

littletwig.com 1.866.lil.twig

Kittrich Corporation

POMONA, CA 91766

(c) 2020. All rights reserved.

MADE IN USA